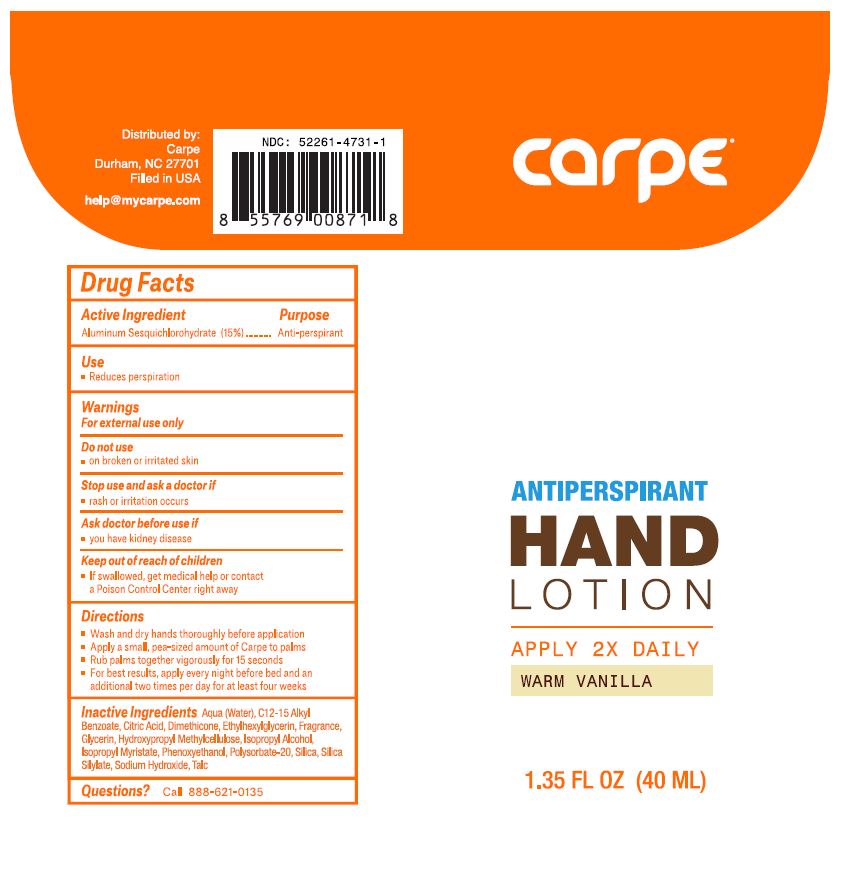 DRUG LABEL: Carpe Antiperspirant Hand Warm Vanilla Scent
NDC: 52261-4731 | Form: Lotion
Manufacturer: Cosco International, Inc.
Category: otc | Type: HUMAN OTC DRUG LABEL
Date: 20231227

ACTIVE INGREDIENTS: Aluminum Sesquichlorohydrate 0.15 kg/1 kg
INACTIVE INGREDIENTS: water; isopropyl alcohol; SILICON DIOXIDE; HEXAMETHYLDISILAZANE; talc; polysorbate 20; dimethicone 350; ALKYL (C12-15) BENZOATE; phenoxyethanol; ISOPROPYL MYRISTATE; glycerin; HYPROMELLOSE 2208 (100000 MPA.S); sodium hydroxide; citric acid monohydrate; ethylhexylglycerin

Drug Facts

Active Ingredient Purpose
Aluminum Sesquicholorhydrate 15% .......................Anti-perspirant

PURPOSE

Anti-perspirant

Use

- Reduces perspiration

Warnings

For external use only

Do not use

- on broken or irritated skin

Stop use and ask a doctor if

- rash or irritation occurs

Ask doctor before use if

- you have kidney disease

Keep out of reach of children

- If swallowed, get medical help or contact a Poison Control Center right away

Directions

- Wash and dry hands throughly before application
- Apply a small, pea-sized amount of Carpe to palms
- Rub palms together vigorously for 15 seconds
- For best results, apply every night before bed and an additional two times per day for at least four weeks

Inactive ingredients

Aqua (Water), C12-15 Alkyl Benzoate, Citric Acid, Dimethicone, Ethylhexylglycerin, Fragrance, Glycerin, Hydroxypropyl Methylcellulose, Isopropyl Alcohol, Isopropyl Myristate, Phenoxyethanol, Polysorbate-20, Silica, Silica Silylate, Sodium Hydroxide, Talc

Questions?

Call 888-621-0135